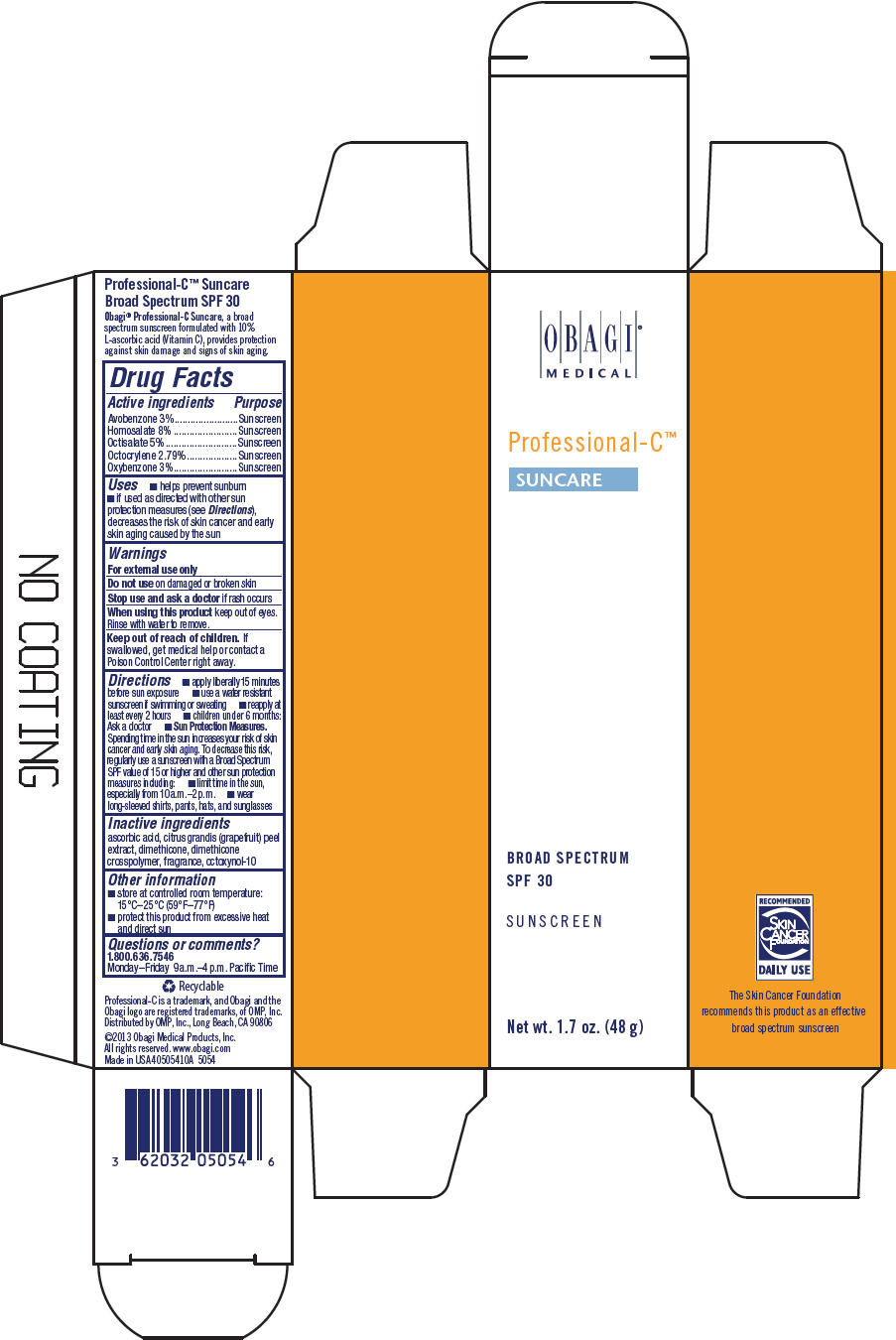 DRUG LABEL: Professional-C Suncare Broad Spectrum SPF 30
NDC: 62032-128 | Form: CREAM
Manufacturer: Obagi Medical Products, Inc., a division of Valeant Pharmaceuticals North America LLC.
Category: otc | Type: HUMAN OTC DRUG LABEL
Date: 20171219

ACTIVE INGREDIENTS: AVOBENZONE 30 mg/1 g; HOMOSALATE 80 mg/1 g; OCTISALATE 50 mg/1 g; OCTOCRYLENE 27.9 mg/1 g; OXYBENZONE 30 mg/1 g
INACTIVE INGREDIENTS: ASCORBIC ACID; CITRUS MAXIMA FRUIT RIND; DIMETHICONE 100; OCTOXYNOL-9

Professional-C™ Suncare Broad Spectrum SPF 30
Sunscreen

Drug Facts

ACTIVE INGREDIENT

Active ingredients | Purpose
Avobenzone 3% | Sunscreen
Homosalate 8% | Sunscreen
Octisalate 5% | Sunscreen
Octocrylene 2.79% | Sunscreen
Oxybenzone 3% | Sunscreen

Uses

- helps prevent sunburn
- if used as directed with other sun protection measures (see Directions), decreases the risk of skin cancer and early skin aging caused by the sun

Warnings

For external use only

Do not use on damaged or broken skin

Stop use and ask a doctor if rash occurs

When using this product keep out of eyes. Rinse with water to remove.

Keep out of reach of children. If swallowed, get medical help or contact a Poison Control Center right away.

Directions

- apply liberally 15 minutes before sun exposure
- use a water resistant sunscreen if swimming or sweating
- reapply at least every 2 hours
- children under 6 months: Ask a doctor
- Sun Protection Measures. Spending time in the sun increases your risk of skin cancer and early skin aging. To decrease this risk, regularly use a sunscreen with a Broad Spectrum SPF value of 15 or higher and other sun protection measures including:
  - limit time in the sun, especially from 10 a.m.–2 p.m.
  - wear long-sleeved shirts, pants, hats, and sunglasses

Inactive ingredients

ascorbic acid, citrus grandis (grapefruit) peel extract, dimethicone, dimethicone crosspolymer, fragrance, octoxynol-10

Other information

- store at controlled room temperature: 15°C–25°C (59°F–77°F)
- protect this product from excessive heat and direct sun

Questions or comments?

1.800.636.7546

Monday–Friday 9 a.m.–4 p.m. Pacific Time

Distributed by OMP, Inc., Long Beach, CA 90806

PRINCIPAL DISPLAY PANEL - 48 g Tube Carton

OBAGI®

MEDICAL

Professional-C™

SUNCARE

BROAD SPECTRUM

SPF 30

SUNSCREEN

Net wt. 1.7 oz. (48 g)